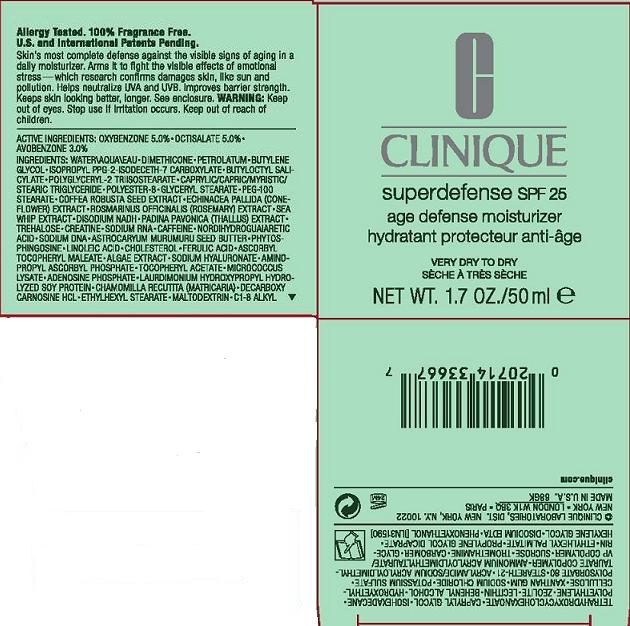 DRUG LABEL: SUPER DEFENSE
NDC: 49527-708 | Form: CREAM
Manufacturer: CLINIQUE LABORATORIES INC
Category: otc | Type: HUMAN OTC DRUG LABEL
Date: 20110628

ACTIVE INGREDIENTS: OXYBENZONE 5.0 mL/100 mL; OCTISALATE 5.0 mL/100 mL; AVOBENZONE 3.0 mL/100 mL
INACTIVE INGREDIENTS: WATER; DIMETHICONE; PETROLATUM; BUTYLENE GLYCOL; BUTYLOCTYL SALICYLATE; POLYGLYCERYL-4 ISOSTEARATE; MEDIUM-CHAIN TRIGLYCERIDES; GLYCERYL MONOSTEARATE; PEG-100 STEARATE; ROBUSTA COFFEE BEAN; ECHINACEA PALLIDA; ROSEMARY; PSEUDOPTEROGORGIA ELISABETHAE; SACCHAROMYCES LYSATE; TREHALOSE; CREATINE; CAFFEINE; MASOPROCOL; ASTROCARYUM MURUMURU SEED BUTTER; LINOLEIC ACID; CHOLESTEROL; LAMINARIA DIGITATA; HYALURONATE SODIUM; ALPHA-TOCOPHEROL ACETATE; ADENOSINE PHOSPHATE DISODIUM; MATRICARIA RECUTITA; ETHYLHEXYL STEARATE; CAPRYLYL GLYCOL; ISOHEXADECANE; LECITHIN, SOYBEAN; DOCOSANOL; XANTHAN GUM; POTASSIUM SULFATE; POLYSORBATE 80; STEARETH-21; SUCROSE; TROMETHAMINE; CARBOMER HOMOPOLYMER TYPE C; GLYCERIN; ETHYLHEXYL PALMITATE; PROPYLENE GLYCOL DICAPRATE; HEXYLENE GLYCOL; EDETATE DISODIUM; PHENOXYETHANOL

ACTIVE INGREDIENT

active ingredients: oxybenzone 5.00% [] octisalate 5.00% [] avobenzone 3.00%

INACTIVE INGREDIENT

inactive ingredients: water [] dimethicone [] petrolatum [] butylene glycol [] butyloctyl salicylate [] polyglyceryl-2 triisostearate [] caprylic/capric/myristic/stearic triglyceride [] polyester-8 [] glyceryl stearate [] peg-100 stearate [] coffea robusta seed extract [] echinacea pallida (coneflower) extract [] rosmarinus officinalis (rosemary) extract [] sea whip extract [] isopropyl ppg-2-isodeceth-7 carboxylate [] padina pavonica (thallus) extract [] micrococcus lysate [] disodium nadh [] trehalose [] creatine [] sodium rna [] caffeine [] nordihydroguaiaretic acid [] sodium dna [] astrocaryum murumuru seed butter [] phytosphingosine [] linoleic acid [] cholesterol [] ascorbyl tocopheryl maleate [] algae extract [] sodium hyaluronate [] aminopropyl ascorbyl phosphate [] tocopheryl acetate [] adenosine phosphate [] laurdimonium hydroxypropyl hydrolyzed soy protein [] chamomilla recutita (matricaria) [] decarboxy carnosine hcl [] ethylhexyl stearate [] caprylyl glycol [] isohexadecane [] polyethylene [] zeolite [] lecithin [] behenyl alcohol [] xanthan gum [] potassium sulfate [] polysorbate 80 [] steareth-21 [] acrylamide/sodium acryloyldimethyltaurate copolymer [] ammonium acryloyldimethyltaurate/vp copolymer [] sucrose [] tromethamine [] carbomer [] glycerin [] ethylhexyl palmitate [] arginine ferulate [] propylene glycol dicaprate [] hexylene glycol [] disodium edta [] phenoxyethanol

WARNINGS

warning: keep out of eyes. discontinue use if irritation occurs. keep out of reach of children.

PACKAGE LABEL

principal display panel:

CLINIQUE

SUPERDEFENSE

AGE DEFENSE MOISTURIZER

FOR VERY DRY TO DRY SKIN

1.7 OZ/ 50 ML

clinique laboratories distr

new york, ny 10022